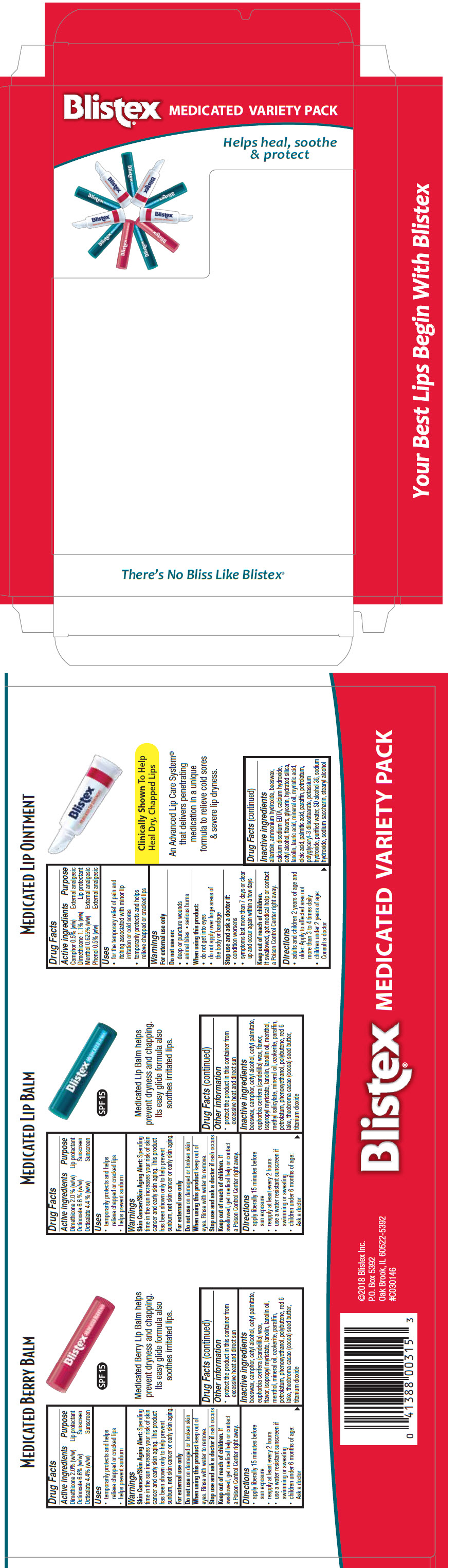 DRUG LABEL: Blistex Medicated Lip Balm Variety Pack (Blistex Medicated Berry Lip Balm, Blistex Medicated Lip Balm, Blistex Medicated Lip)
NDC: 10157-9910 | Form: KIT | Route: TOPICAL
Manufacturer: Blistex Inc
Category: otc | Type: HUMAN OTC DRUG LABEL
Date: 20241216

ACTIVE INGREDIENTS: Dimethicone 2 g/100 g; Octinoxate 6.6 g/100 g; Octisalate 4.4 g/100 g; Dimethicone 2 g/100 g; Octinoxate 6.6 g/100 g; Octisalate 4.4 g/100 g; Dimethicone 1.1 g/100 g; Camphor (Synthetic) 0.5 g/100 g; Menthol, Unspecified Form 0.625 g/100 g; Phenol 0.5 g/100 g
INACTIVE INGREDIENTS: MINERAL OIL; PETROLATUM; CERESIN; CANDELILLA WAX; LANOLIN OIL; YELLOW WAX; ISOPROPYL MYRISTATE; LANOLIN; POLYBUTENE (1400 MW); CETYL PALMITATE; CETYL ALCOHOL; PARAFFIN; COCOA BUTTER; MENTHOL, UNSPECIFIED FORM; PHENOXYETHANOL; .ALPHA.,.ALPHA.-DIBROMO-D-CAMPHOR; TITANIUM DIOXIDE; D&C RED NO. 6; MINERAL OIL; PETROLATUM; CERESIN; CANDELILLA WAX; LANOLIN OIL; YELLOW WAX; ISOPROPYL MYRISTATE; LANOLIN; POLYBUTENE (1400 MW); CETYL PALMITATE; CETYL ALCOHOL; PARAFFIN; COCOA BUTTER; MENTHOL, UNSPECIFIED FORM; PHENOXYETHANOL; .ALPHA.,.ALPHA.-DIBROMO-D-CAMPHOR; METHYL SALICYLATE; TITANIUM DIOXIDE; D&C RED NO. 6; WATER; MINERAL OIL; YELLOW WAX; PETROLATUM; LANOLIN; POLYGLYCERYL-3 DIISOSTEARATE; PARAFFIN; ALCOHOL; AMMONIA; GLYCERIN; ALLANTOIN; PEPPERMINT OIL; HYDRATED SILICA; PALMITIC ACID; CETYL ALCOHOL; STEARYL ALCOHOL; CALCIUM HYDROXIDE; LAURIC ACID; MYRISTIC ACID; SODIUM HYDROXIDE; OLEIC ACID; EDETATE CALCIUM DISODIUM ANHYDROUS; POTASSIUM HYDROXIDE

Blistex® Medicated Lip Balm Variety Pack (Blistex® Medicated Berry Lip Balm, Blistex® Medicated Lip Balm, Blistex® Medicated Lip Ointment)

MEDICATED BERRY BALM

Drug Facts

ACTIVE INGREDIENT

Active ingredients | Purpose
Dimethicone 2.0% (w/w) | Lip protectant
Octinoxate 6.6% (w/w) | Sunscreen
Octisalate 4.4% (w/w) | Sunscreen

Uses

- temporarily protects and helps relieve chapped or cracked lips
- helps prevent sunburn

Warnings

Skin Cancer/Skin Aging Alert

Spending time in the sun increases your risk of skin cancer and early skin aging. This product has been shown only to help prevent sunburn, not skin cancer or early skin aging.

For external use only

Do not use on damaged or broken skin

When using this product keep out of eyes. Rinse with water to remove.

Stop use and ask a doctor if rash occurs

Keep out of reach of children. If swallowed, get medical help or contact a Poison Control Center right away.

Directions

- apply liberally 15 minutes before sun exposure
- reapply at least every 2 hours
- use a water resistant sunscreen if swimming or sweating
- children under 6 months of age: Ask a doctor

Other information

- protect the product in this container from excessive heat and direct sun

Inactive ingredients

beeswax, camphor, cetyl alcohol, cetyl palmitate, euphorbia cerifera (candelilla) wax, flavor, isopropyl myristate, lanolin, lanolin oil, menthol, mineral oil, ozokerite, paraffin, petrolatum, phenoxyethanol, polybutene, red 6 lake, theobroma cacao (cocoa) seed butter, titanium dioxide

MEDICATED LIP BALM

Drug Facts

ACTIVE INGREDIENT

Active ingredients | Purpose
Dimethicone 2.0 % (w/w) | Lip protectant
Octinoxate 6.6 % (w/w) | Sunscreen
Octisalate 4.4 % (w/w) | Sunscreen

Uses

- temporarily protects and helps relieve chapped or cracked lips
- helps prevent sunburn

Warnings

Skin Cancer/Skin Aging Alert

Spending time in the sun increases your risk of skin cancer and early skin aging. This product has been shown only to help prevent sunburn, not skin cancer or early skin aging.

For external use only

Do not use on damaged or broken skin

When using this product keep out of eyes. Rinse with water to remove.

Stop use and ask a doctor if rash occurs

Keep out of reach of children. If swallowed, get medical help or contact a Poison Control Center right away.

Directions

- apply liberally 15 minutes before sun exposure
- reapply at least every 2 hours
- use a water resistant sunscreen if swimming or sweating
- children under 6 months of age: Ask a doctor

Other information

- protect the product in this container from excessive heat and direct sun

Inactive ingredients

beeswax, camphor, cetyl alcohol, cetyl palmitate, euphorbia cerifera (candelilla) wax, flavor, isopropyl myristate, lanolin, lanolin oil, menthol, methyl salicylate, mineral oil, ozokerite, paraffin, petrolatum, phenoxyethanol, polybutene, red 6 lake, theobroma cacao (cocoa) seed butter, titanium dioxide

MEDICATED LIP OINTMENT

Drug Facts

ACTIVE INGREDIENT

Active ingredients | Purpose
Camphor 0.5% (w/w) | External analgesic
Dimethicone 1.1% (w/w) | Lip protectant
Menthol 0.625% (w/w) | External analgesic
Phenol 0.5% (w/w) | External analgesic

Uses

- for the temporary relief of pain and itching associated with minor lip irritation or cold sores
- temporarily protects and helps relieve chapped or cracked lips

Warnings

For external use only

Do not use on

- deep or puncture wounds
- animal bites
- serious burns

When using this product

- do not get into eyes
- do not apply over large areas of the body or bandage

Stop use and ask a doctor if

- condition worsens
- symptoms last more than 7 days or clear up and occur again within a few days

Keep out of reach of children.

If swallowed, get medical help or contact a Poison Control Center right away.

Directions

- adults and children 2 years of age and older: Apply to affected area not more than 3 to 4 times daily
- children under 2 years of age: Consult a doctor

Inactive ingredients

allantoin, ammonium hydroxide, beeswax, calcium disodium EDTA, calcium hydroxide, cetyl alcohol, flavors, glycerin, hydrated silica, lanolin, lauric acid, mineral oil, myristic acid, oleic acid, palmitic acid, paraffin, petrolatum, polyglyceryl-3 diisostearate, potassium hydroxide, purified water, SD alcohol 36, sodium hydroxide, sodium saccharin, stearyl alcohol

PRINCIPAL DISPLAY PANEL - Kit Carton

Blistex® MEDICATED VARIETY PACK

Helps heal, soothe
& protect

There's No Bliss Like Blistex®